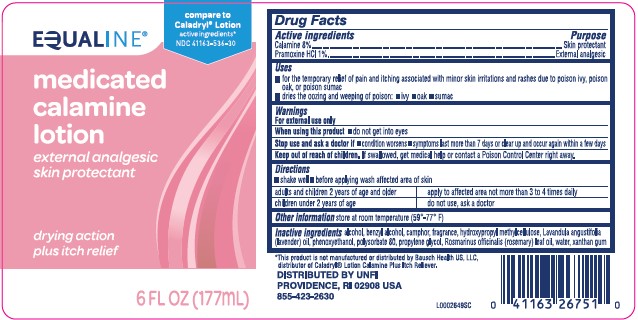 DRUG LABEL: Calamine
NDC: 41163-536 | Form: LOTION
Manufacturer: United Natural Foods, Inc. dba UNFI
Category: otc | Type: HUMAN OTC DRUG LABEL
Date: 20260217

ACTIVE INGREDIENTS: FERRIC OXIDE RED 80 mg/1 mL; PRAMOXINE HYDROCHLORIDE 10 mg/1 mL
INACTIVE INGREDIENTS: ALCOHOL; BENZYL ALCOHOL; CAMPHOR (NATURAL); HYPROMELLOSE, UNSPECIFIED; LAVENDER OIL; PHENOXYETHANOL; POLYSORBATE 80; PROPYLENE GLYCOL; ROSEMARY OIL; WATER; XANTHAN GUM

Equaline 336.003/336AG
Medicated Calamine Lotion

Active ingredients

Calamine 8%

Pramoxine HCl 1%

Purpose

Skin protectant

External analgesic

Use

- for the temporary relief of pain and itching associated with minor skin irritations and rashes due to poison ivy, poison oak, or poison sumac
- dries the oozing and weeping of poison:
- ivy
- oak
- sumac

Warnings

For external use only

When using this product

- do not get into eyes

Stop use and ask a doctor

- condition worsens
- symptoms last more than 7 days or clear up and occur again within a few days

Keep out of reach of children.

If swallowed, get medical help or contact a Poison Control Center right away.

Directions

- shake well
- before applying was affected are of skin

Adults and children 2 years of age and older - apply to affected area not more than 3 to 4 times daily

Children under 2 years of age - do not use, ask a doctor

Other information

store at room temperature (59°-77°F)

Inactive ingredients

alcohol, benzyl alcohol, camphor, fragrance, hydroxypropyl methylcellulose, Lavandula angustifolia (lavender) oil, phenoxyethanol, polysorbate 80, propylene glycol, Rosmarinus officinalis (rosemary) leaf oil, water, xanthan gum

Disclaimer

*This product is not manufactured or distributed by Bausch Health US, LLA, distributor of CaladrylLotion Calamine Plus Itch Reliever.

ADVERSE REACTION

DISTRIBUTED BY UNFI

PROVIDENCE, RI 02908 USA

855-423-2630

Principal display panel

Compare to Caladryl®Lotion active ingredient*

NDC 41163-536-30

EQUALINE®

medicated calamine lotion

external analgesic

skin protectant

drying action plus itch relief

6 FL OZ (177 mL)